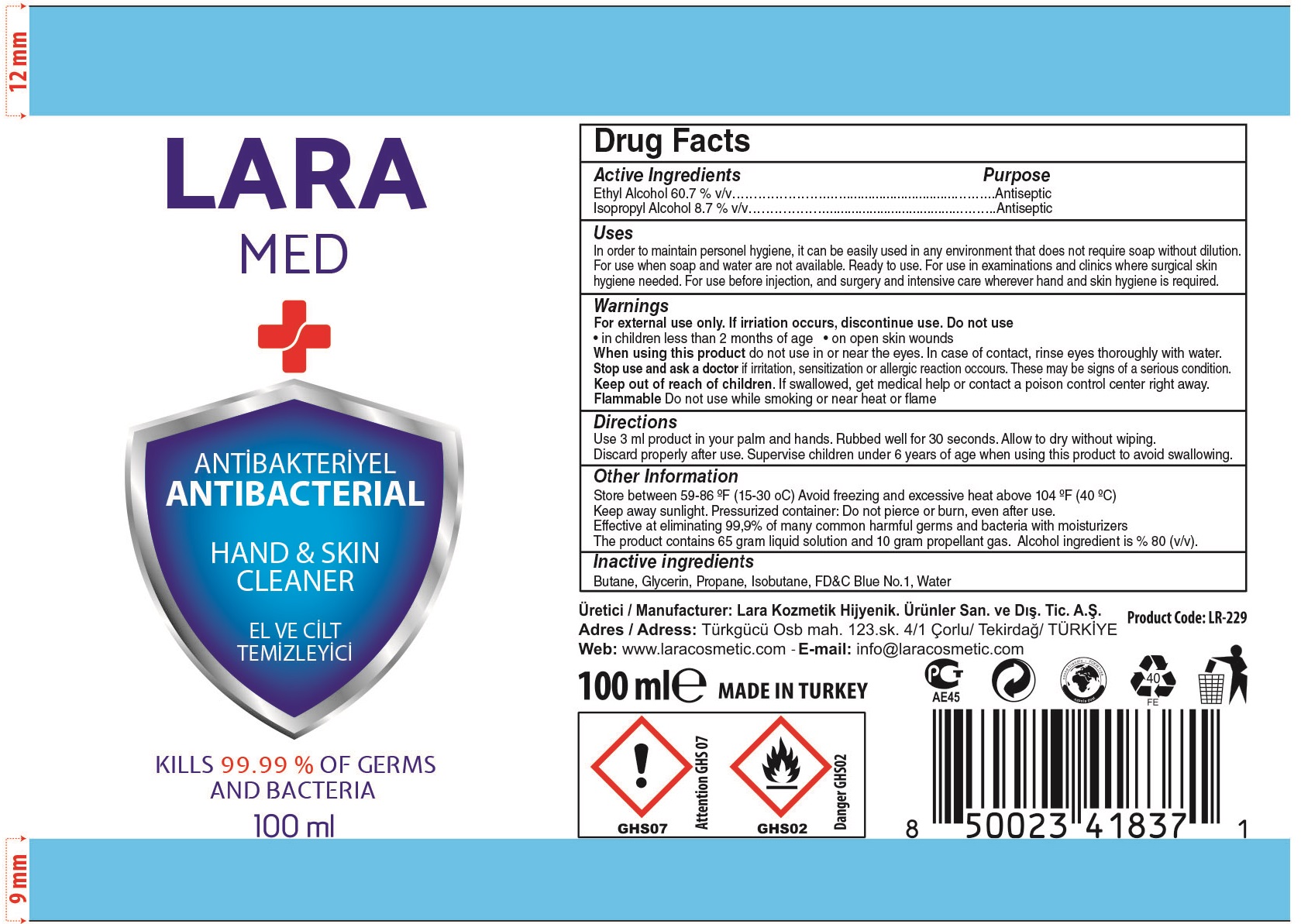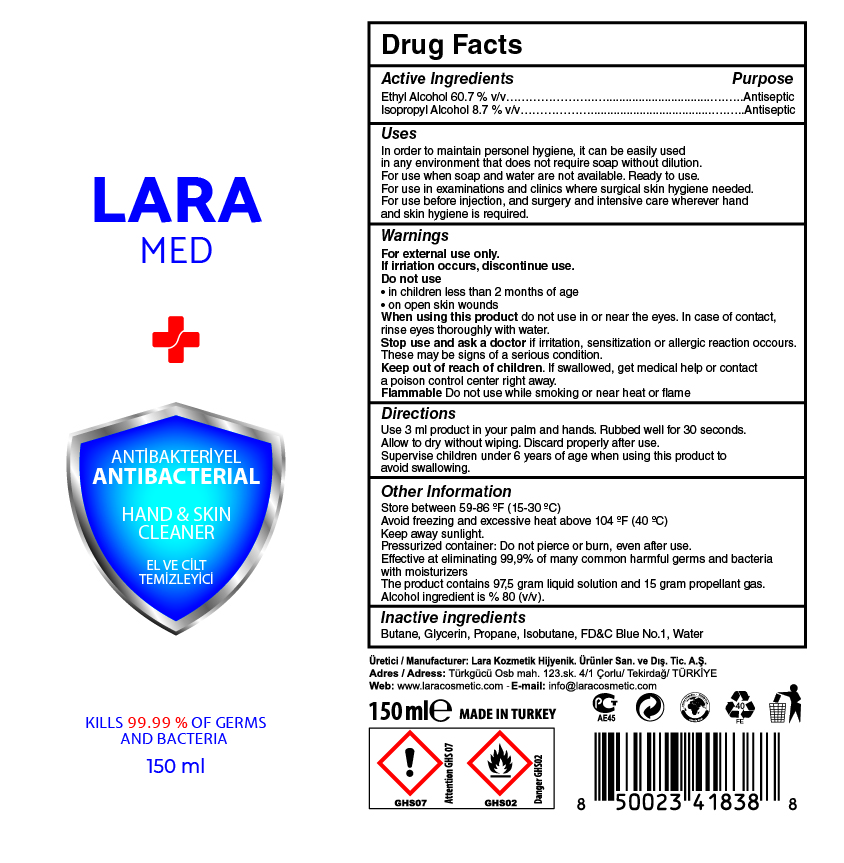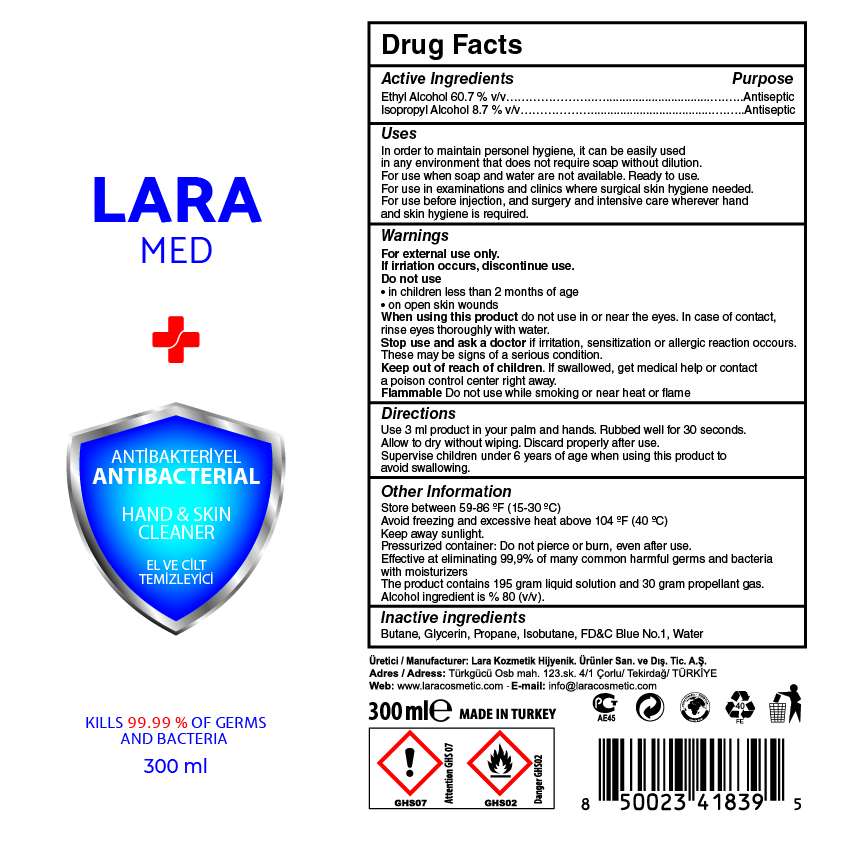 DRUG LABEL: LARA MED Antibacterial Hand Skin Cleaner
NDC: 86994-006 | Form: AEROSOL, SPRAY
Manufacturer: LARA KOZMETIK HIJYENIK URUNLERI SANAYI VE DIS TICARET ANONIM SIRKETI
Category: otc | Type: HUMAN OTC DRUG LABEL
Date: 20201011

ACTIVE INGREDIENTS: ALCOHOL 60.7 mL/100 mL; ISOPROPYL ALCOHOL 8.7 mL/100 mL
INACTIVE INGREDIENTS: GLYCERIN 1.3 mL/100 mL; FD&C BLUE NO. 1 0.0001 mL/100 mL; WATER 24.2999 mL/100 mL; BUTANE 3.25 mL/100 mL; ISOBUTANE 0.875 mL/100 mL; PROPANE 0.875 mL/100 mL

LARA MED ANTIBACTERIAL HAND&SKIN CLEANER

This is a hand sanitizer manufactured according to the Temporary Policy for Preparation of Certain Alcohol-Based Hand Sanitizer Products During the Public Health Emergency (CoViD-19); Guidance for Industry.

The hand sanitizer is manufactured using only the following United States Pharmacopoeia (USP) grade ingredients in the preparation of the product (percentage in final product formulation) consistent with World Health Organization (WHO) recommendations:

1. Alcohol (ethanol) (USP or Food Chemical Codex (FCC) grade) (60.7%, volume/volume(v/v)) in an aqueous solution denatured according to Alcohol and Tobacco Tax and Trade Bureau regulations in 27 CFR part 20.
2. Isopropyl Alcohol 8.7% (v/v)
3. Glycerol (1.3% (v/v)
4. BUTANE (3.25% (v/v)
5. PROPANE (0.875% (v/v)
6. ISOBUTANE (0.875% (v/v)
7. FD&C Blue No.1 (0.0001% (v/v)
8. Sterile distilled water or boiled cold water.

The firm does not add other active or inactive ingredients. Different or additional ingredients may impact the quality and potency of the product.

Active Ingredient(s)

Alcohol 60.7% v/v. Purpose: Antiseptic

Isopropyl Alcohol 8.7% v/v. Purpose: Antiseptic

Purpose

Antiseptic, Hand Sanitizer

Use

In order to maintain personel hygiene, it can be easily used in any environment that does not require soap without dilution.

For use when soap and water are not available. Ready to use. For use in examinations and clinics where surgical skin hygiene needed. For use before injection, and surgery and intensive care wherever hand and skin hygiene is required.

Warnings

For external use only. If irritation occurs, discontinue use.

Do not use

- in children less than 2 months of age
- on open skin wounds

When using this product do not use in or near the eyes. In case of contact with eyes, rinse eyes thoroughly with water.
Stop use and ask a doctor if irritation, sensitization or allergin reaction occurs. These may be signs of a serious condition.
Keep out of reach of children. If swallowed, get medical help or contact a Poison Control Center right away.

Flammable Do not use while smoking or near heat or flame

Stop use and ask a doctor if irritation or rash occurs. These may be signs of a serious condition.

Keep out of reach of children. If swallowed, get medical help or contact a Poison Control Center right away.

Directions

- use 3 ml product in your palm and hands. Rubbed well for 30 seconds. Allow to dry without wiping. Discard properly after use.
- Supervise children under 6 years of age when using this product to avoid swallowing.

Other information

- Store between 15-30C (59-86F)
- Avoid freezing and excessive heat above 40C (104F)
- Keep away sunlight.
- Pressurized container: Do not pierce or burn, even after use.

Inactive ingredients

Butane, Glycerol, Propane, Isobutane, FD&C Blue No.1, Water

Package Label - Principal Display Panel

100 mL NDC:86994-006-01

86994-006-02 NDC - 150 ml

86994-006-03 NDC - 300 ml